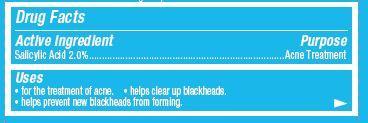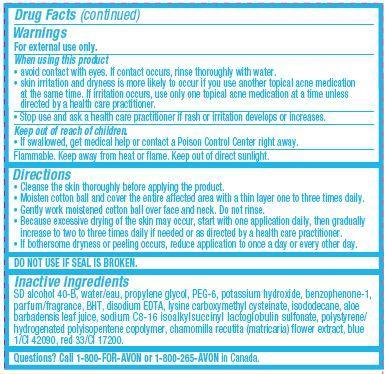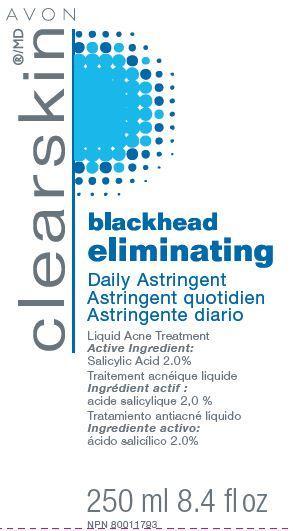 DRUG LABEL: Clearskin Blackhead Eliminating
NDC: 10096-0320 | Form: LIQUID
Manufacturer: New Avon LLC
Category: otc | Type: HUMAN OTC DRUG LABEL
Date: 20160219

ACTIVE INGREDIENTS: Salicylic Acid 20 mg/1 mL

Active ingredient

Salicylic Acid 2.0%.......................

Purpose
........................Acne Treatment

Uses

- for the treatment of acne
- helps clear up blackheads
- helps prevent new blackheads from forming

Warnings

For external use only.

When using this product

- avoid contact with eyes. If contact occurs, rinse thoroughly with water.
- skin irritation and dryness is more likely to occur if you use another topical acne medication at the same time. If irritation occurs, use only one topical acne medication at a time unless directed by a health care practitioner.

Stop use and ask a health care practitioner if rash or irritation develops or increases.

Keep out of reach of children

- If swallowed, get medical help or contact a Poison Control Center right away.

GENERAL PRECAUTIONS

Flammable. Keep away from heat or flame. Keep out of direct sunlight.

Directions

- Cleanse the skin thoroughly before applying the product.

- Moisten cotton ball and cover the entire affected area with a thin layer one to three times daily.

- Gently work moistened cotton ball over face and neck. Do not rinse.

- Because excessive drying of the skin may occur, start with one application daily, then gradually increase to two to three times daily if needed or as directed by a health care practitioner.

- If bothersome dryness or peeling occurs, reduce application to once a day or every other day.

DO NOT USE IF SEAL IS BROKEN.

INACTIVE INGREDIENT

Inactive ingredients SD alcohol 40-B, water/eau, propylene glycol, PEG-6, potassium hydroxide, benzophenone-1, parfum/fragrance, BHT, disodium EDTA, lysine carboxymethyl cysteinate, isododecane, aloe barbadensis leaf juice, sodium C8-16 isoalkylsuccinyl lactoglobulin sulfonate, polystyrene/
hydrogenated polyisopentene copolymer, chamomilla recutita (matricaria) flower extract, blue 1/CI 42090, red 33/CI 17200.

QUESTIONS

Questions? Call 1-800-FOR-AVON or 1-800-265-AVON in Canada.